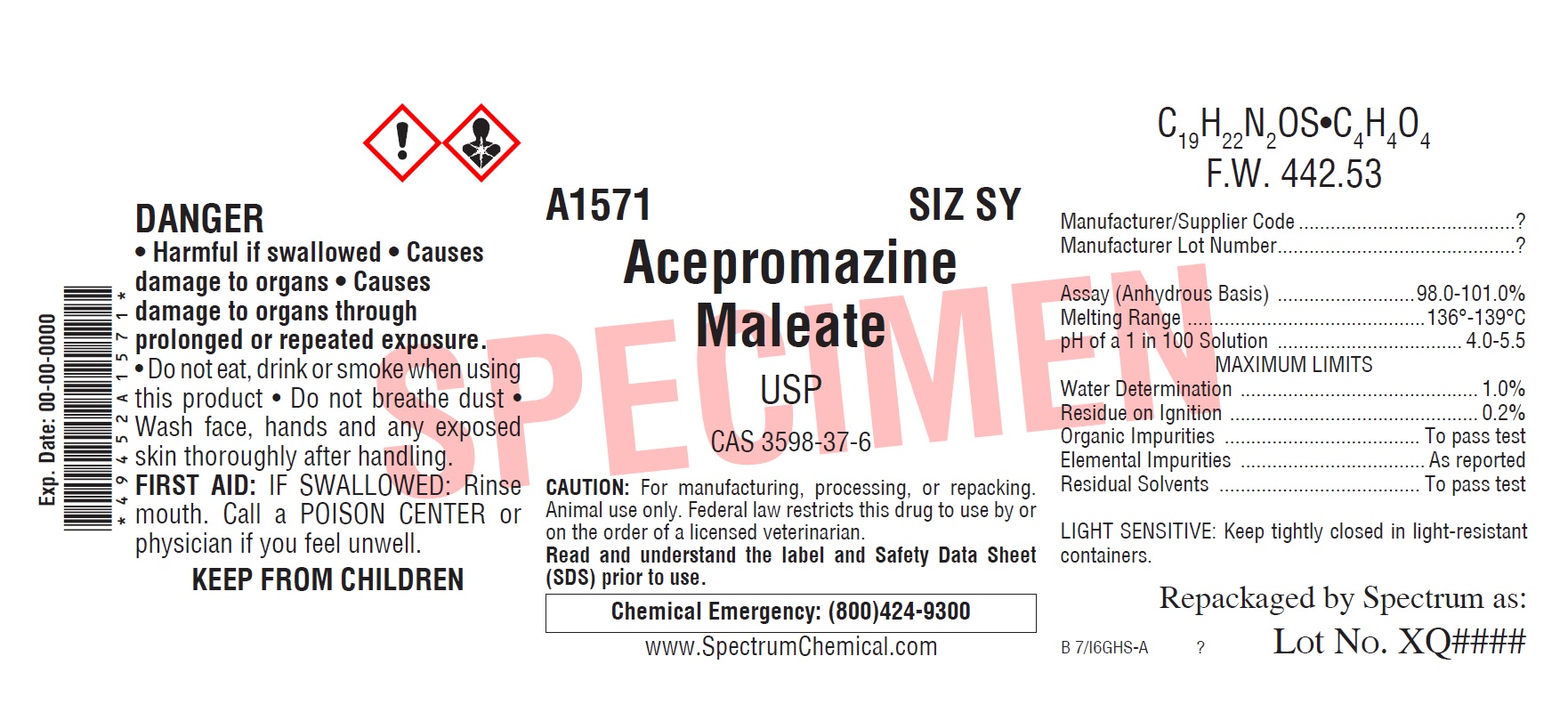 DRUG LABEL: Acepromazine Maleate
NDC: 49452-0007 | Form: POWDER
Manufacturer: Spectrum Laboratory Products, Inc.
Category: other | Type: BULK INGREDIENT
Date: 20210126

ACTIVE INGREDIENTS: ACEPROMAZINE MALEATE 1 g/1 g

Acepromazine Maleate